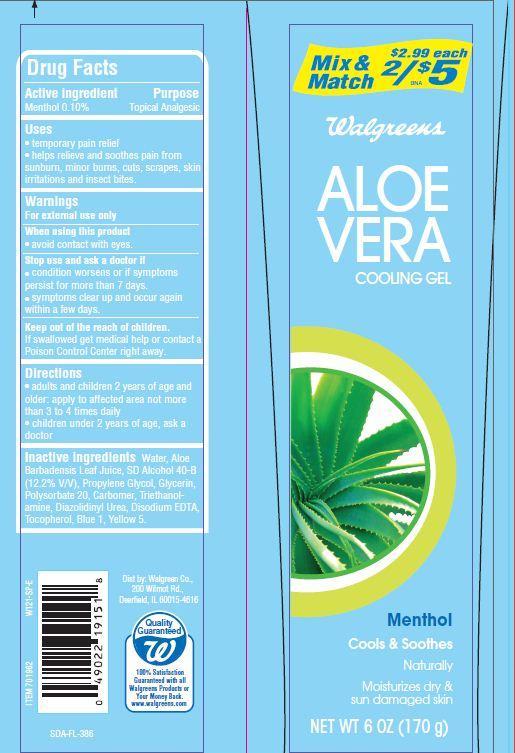 DRUG LABEL: Walgreens
NDC: 0363-4002 | Form: GEL
Manufacturer: WALGREEN CO.
Category: otc | Type: HUMAN OTC DRUG LABEL
Date: 20121204

ACTIVE INGREDIENTS: MENTHOL 0.1 g/100 g
INACTIVE INGREDIENTS: ALOE VERA LEAF; FD&C BLUE NO. 1; DIAZOLIDINYL UREA; EDETATE DISODIUM; GLYCERIN; POLYSORBATE 20; PROPYLENE GLYCOL; TOCOPHEROL; TROLAMINE; WATER; FD&C YELLOW NO. 5

Drug Facts

Active ingredients

Menthol 0.10%

PURPOSE

Topical Analgesic

Uses

- temporary pain relief
- helps relieve and soothes pain from sunburn, minor burns, cuts, scrapes, skin irritations and insect bites

Warnings

For external use only

When using this product

- avoid contact with eyes.

Stop use and ask a doctor if

- condition worsens or symptoms persist for more than 7 days.
- symptoms clear up and occur again within a few days.

Keep out of reach of children.
If swallowed get medical help or contact Poison Control Center right away.

Directions

- adults and children 2 years of age and older: apply to affected area not more than 3 to 4 times daily
- children under 2 years of age: do not use, ask a doctor

Inactive ingredients

Water, Alcohol Denat., Propylene Glycol, Glycerin, Polysorbate 20, Carbomer, Triethanolamine, Aloe Barbadensis Leaf Juice, Disodium EDTA, Tocopherol, Diazolidinyl Urea, Blue 1, Yellow 5.

Principal Display Panel

Mix and Match
$2.99 each
2/$5
Walgreens
ALOE
VERA
COOLING GEL
Menthol
Cools and Soothes
Naturally
Moisturizes dry and
sun damaged skin
NET WT 6 OZ (170g)